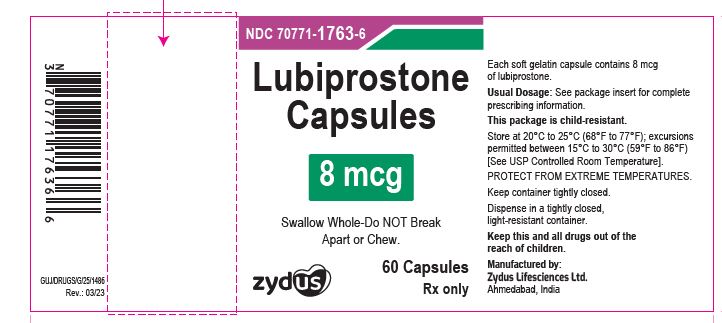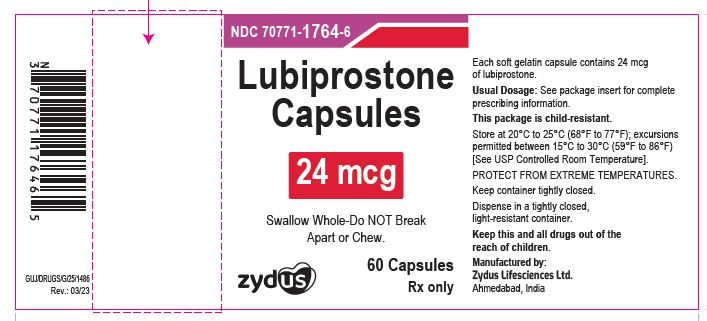 DRUG LABEL: Lubiprostone
NDC: 70771-1763 | Form: CAPSULE
Manufacturer: Zydus Lifesciences Limited
Category: prescription | Type: HUMAN PRESCRIPTION DRUG LABEL
Date: 20241130

ACTIVE INGREDIENTS: LUBIPROSTONE 8 ug/1 1
INACTIVE INGREDIENTS: 1,4-SORBITAN; FERRIC OXIDE RED; FERROSOFERRIC OXIDE; GELATIN, UNSPECIFIED; MEDIUM-CHAIN TRIGLYCERIDES; PROPYLENE GLYCOL; SHELLAC; SORBITOL; TITANIUM DIOXIDE; WATER

Lubiprostone Capsules

PACKAGE LABEL.PRINCIPAL DISPLAY PANEL

NDC 70771-1763-6

Lubiprostone Capsules, 8 mcg

60 Capsules

Rx only

NDC 70771-1764-6

Lubiprostone Capsules, 24 mcg

60 Capsules

Rx only